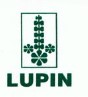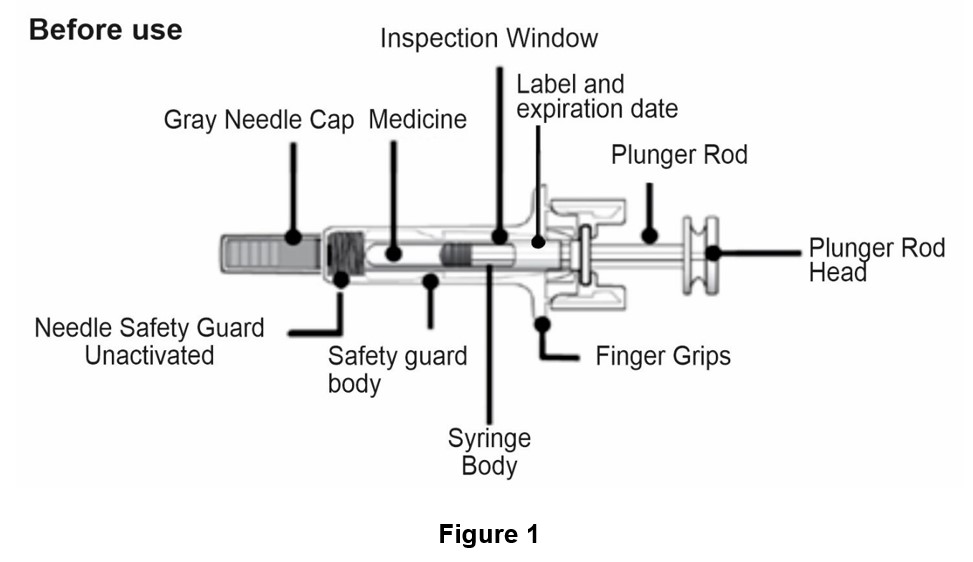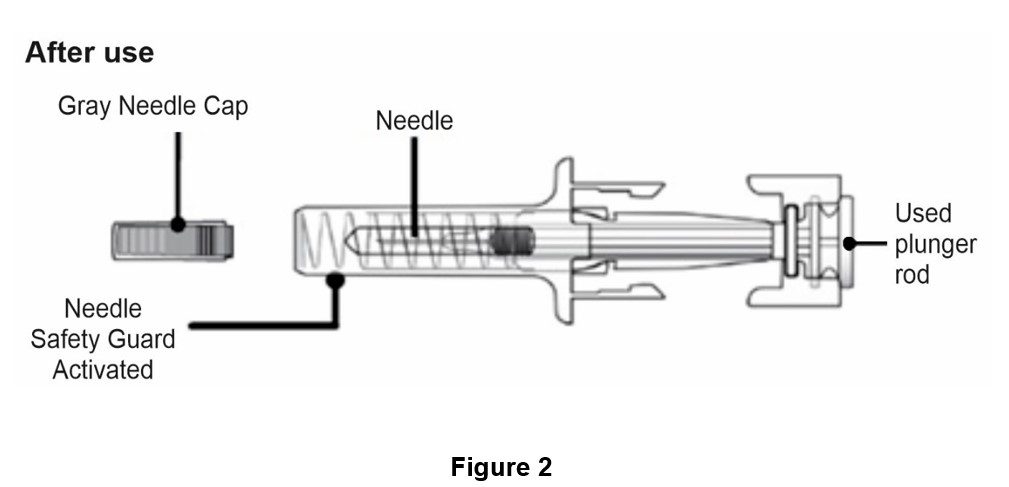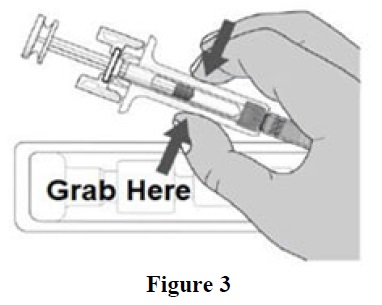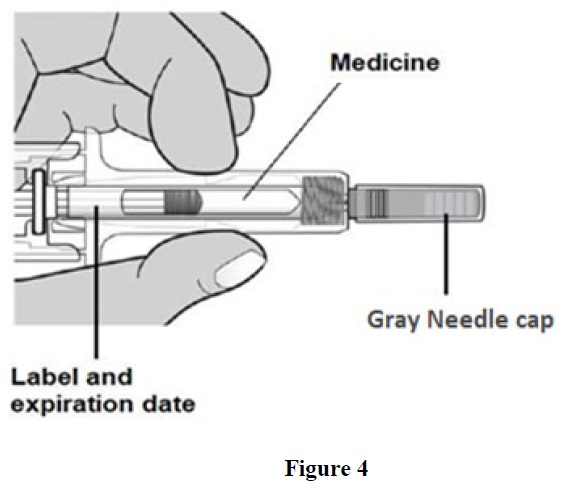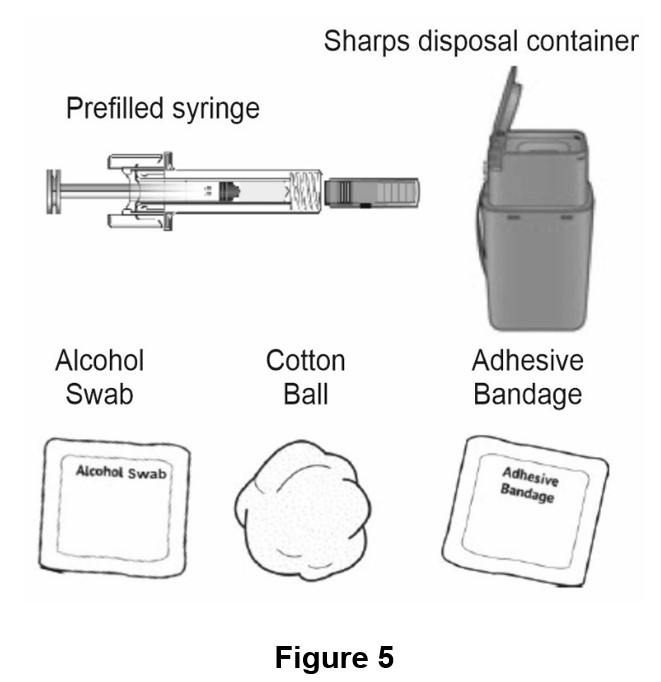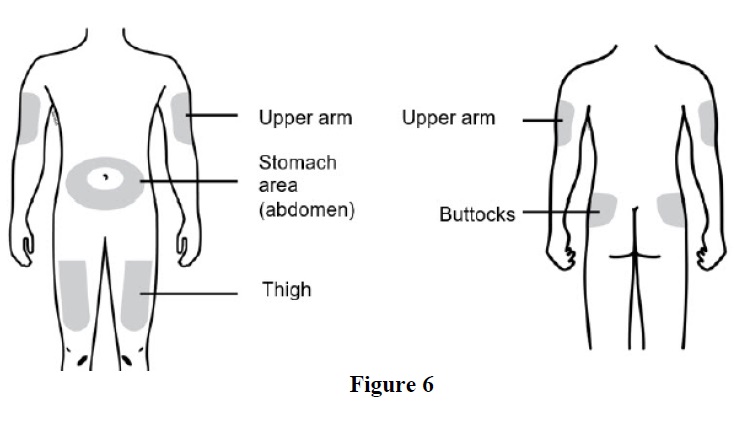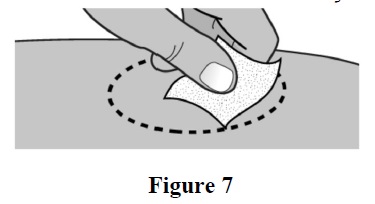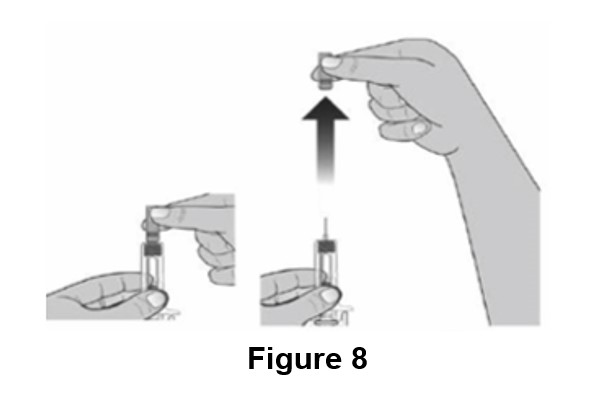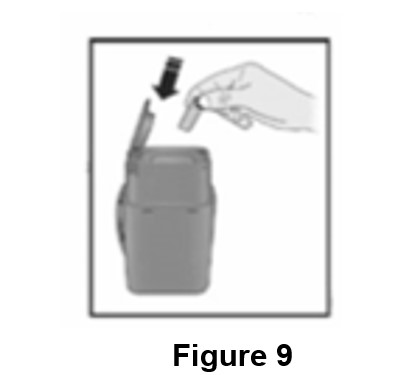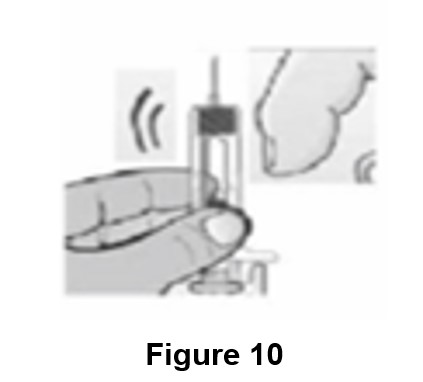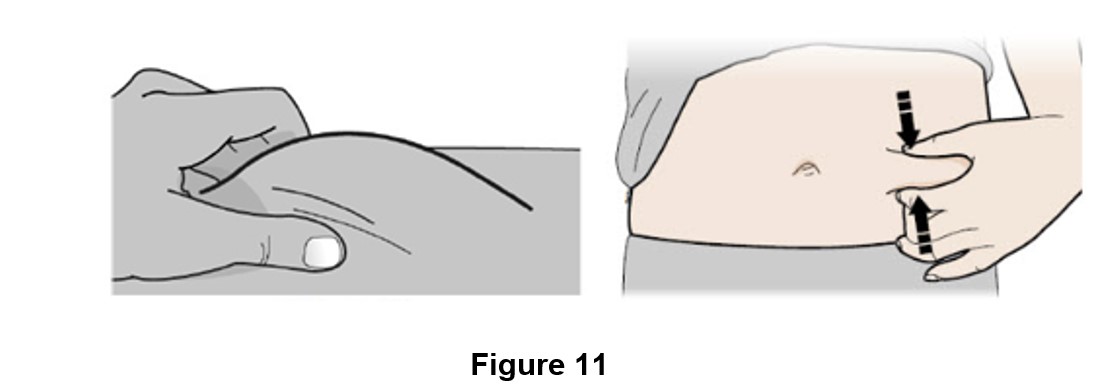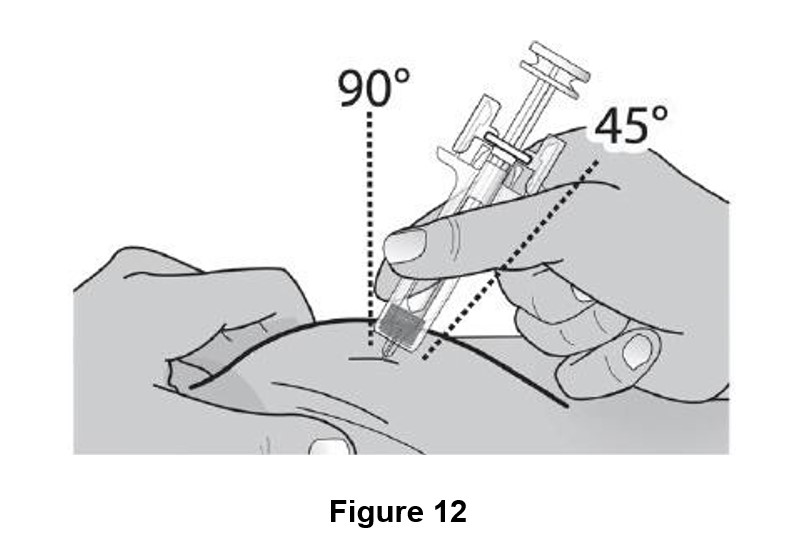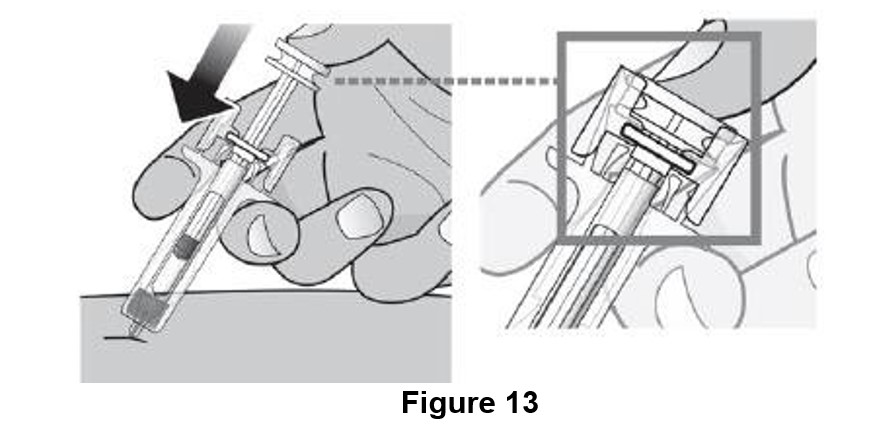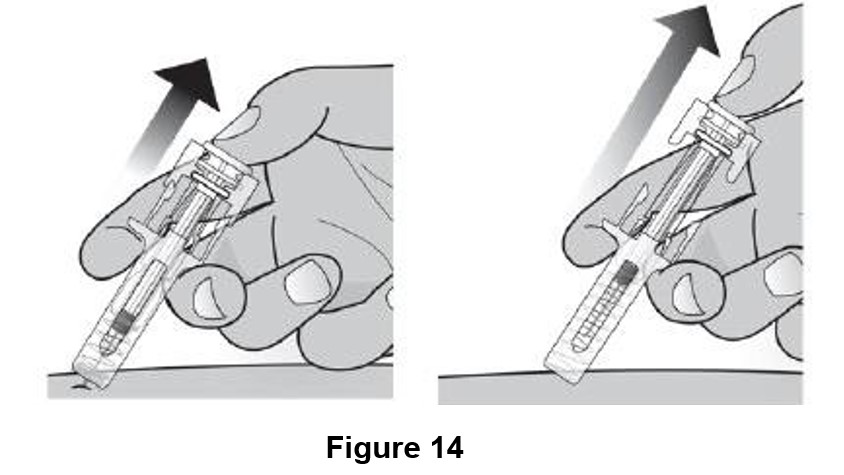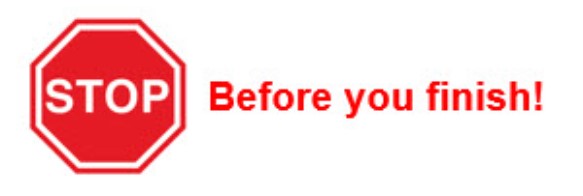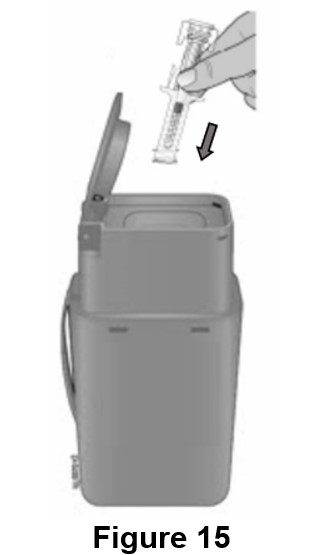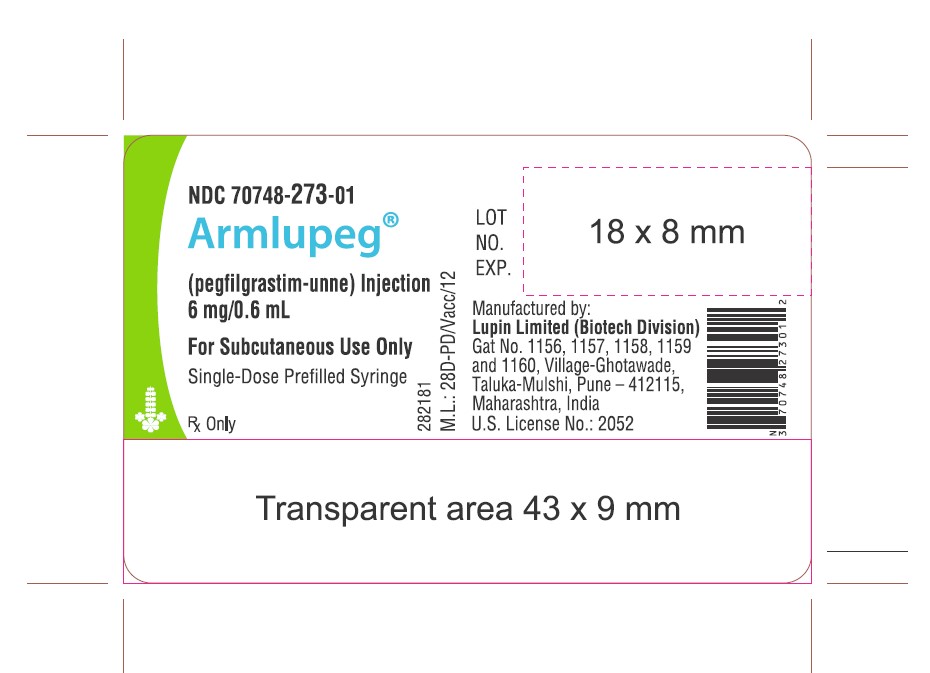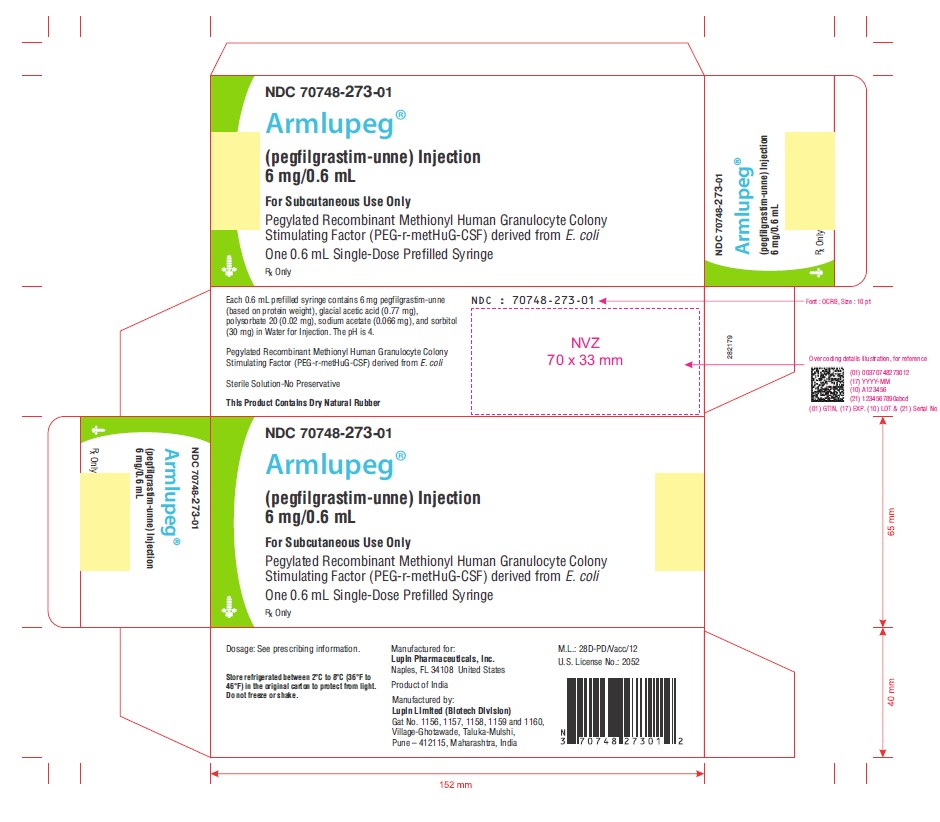 DRUG LABEL: ARMLUPEG
NDC: 70748-273 | Form: INJECTION
Manufacturer: Lupin Pharmaceuticals, Inc.
Category: prescription | Type: HUMAN PRESCRIPTION DRUG LABEL
Date: 20260223

ACTIVE INGREDIENTS: PEGFILGRASTIM 6 mg/0.6 mL
INACTIVE INGREDIENTS: ACETIC ACID 0.77 mg/0.6 mL; POLYSORBATE 20 0.02 mg/0.6 mL; SODIUM ACETATE ANHYDROUS 0.066 mg/0.6 mL; SORBITOL 30 mg/0.6 mL; WATER

HIGHLIGHTS OF PRESCRIBING INFORMATION

These highlights do not include all the information needed to use ARMLUPEG safely and effectively. See full prescribing information for ARMLUPEG.
ARMLUPEG(pegfilgrastim-unne) injection, for subcutaneous use
Initial U.S. Approval: 2025
ARMLUPEG (pegfilgrastim-unne) is biosimilar* to NEULASTA (pegfilgrastim) (1)

1 INDICATIONS AND USAGE

Armlupeg is a leukocyte growth factor indicated to

- Decrease the incidence of infection, as manifested by febrile neutropenia, in patients with non-myeloid malignancies receiving myelosuppressive anti-cancer drugs associated with a clinically significant incidence of febrile neutropenia. (1.1)
- Increase survival in patients acutely exposed to myelosuppressive doses of radiation (Hematopoietic Subsyndrome of Acute Radiation Syndrome). (1.2)

Limitations of Use

Armlupeg is not indicated for the mobilization of peripheral blood progenitor cells for hematopoietic stem cell transplantation.

2 DOSAGE AND ADMINISTRATION

- Patients with cancer receiving myelosuppressive chemotherapy
- For adult patients of any weight and pediatric patients weighing 45 kg and greater, the recommended dosage is 6 mg subcutaneously once per chemotherapy cycle. (2.1)
- Do not administer between 14 days before and 24 hours after administration of chemotherapy. (2.1)
- Patients acutely exposed to myelosuppressive doses of radiation
- For adults of any weight and pediatric patients weighing 45 kg and greater, the recommended dosage is two doses, 6 mg each, subcutaneously one week apart. Administer the first dose as soon as possible after suspected or confirmed exposure to myelosuppressive doses of radiation, and a second dose one week after. (2.2)

3 DOSAGE FORMS AND STRENGTHS

- Injection: 6 mg/0.6 mL solution in a single-dose prefilled syringe for manual use only. (3)

4 CONTRAINDICATIONS

In patients with a history of serious hypersensitivity reaction to pegfilgrastim products or filgrastim products.

5 WARNINGS AND PRECAUTIONS

- Fatal splenic rupture: Evaluate patients who report left upper abdominal or shoulder pain for an enlarged spleen or splenic rupture. (5.1)
- Acute respiratory distress syndrome (ARDS): Evaluate patients who develop fever, lung infiltrates, or respiratory distress. Discontinue Armlupeg in patients with ARDS. (5.2)
- Serious hypersensitivity reactions, including anaphylaxis: Permanently discontinue Armlupeg in patients with serious hypersensitivity reactions. (5.3)
- Fatal sickle cell crises: Discontinue Armlupeg if sickle cell crisis occurs (5.4)
- Glomerulonephritis: Evaluate and consider dose-reduction or interruption of Armlupeg if causality is likely. (5.5)
- Thrombocytopenia: Monitor platelet counts. (5.7)
- Myelodysplastic Syndrome (MDS) and Acute Myeloid Leukemia (AML): Monitor patients with breast and lung cancer using Armlupeg in conjunction with chemotherapy and/or radiotherapy for signs and symptoms of MDS/AML. (5.10)
- Aortitis: Discontinue Armlupeg if aortitis is suspected (5.11)

6 ADVERSE REACTIONS

Most common adverse reactions (≥ 5% difference in incidence compared to placebo) are bone pain and pain in extremity.

To report SUSPECTED ADVERSE REACTIONS, contact Valorum Biologics, LLC at 1-844-576-2709 or FDA at 1-800-FDA-1088 or www.fda.gov/medwatch.

*Biosimilar means that the biological product is approved based on data demonstrating that it is highly similar to an FDA-approved biological product, known as a reference product, and that there are no clinically meaningful differences between the biosimilar product and the reference product. Biosimilarity of Armlupeg has been demonstrated for the condition(s) of use (e.g., indication(s), dosing regimen(s)), strength(s), dosage form(s), and route(s) of administration described in its Full Prescribing Information.

FULL PRESCRIBING INFORMATION

1 INDICATIONS AND USAGE

1.1 Patients with Cancer Receiving Myelosuppressive Chemotherapy

Armlupeg is indicated in adults and pediatric patients aged newborn and older to decrease the incidence of infection, as manifested by febrile neutropenia, in patients with non-myeloid malignancies receiving myelosuppressive anti-cancer drugs associated with a clinically significant incidence of febrile neutropenia [see Clinical Studies (14.1)].

Limitations of Use

Armlupeg is not indicated for the mobilization of peripheral blood progenitor cells for hematopoietic stem cell transplantation.

1.2 Patients with Hematopoietic Subsyndrome of Acute Radiation Syndrome

Armlupeg is indicated to increase survival in adults and pediatric patients aged newborn and older acutely exposed to myelosuppressive doses of radiation [see Dosage and Administration (2.2) and Clinical Studies (14.2)].

2 DOSAGE AND ADMINISTRATION

2.1 Patients with Cancer Receiving Myelosuppressive Chemotherapy

The recommended dosage of Armlupeg for adults of any weight and pediatric patients weighing at least 45 kg with cancer receiving myelosuppressive chemotherapy is a single subcutaneous injection of 6 mg administered once per chemotherapy cycle. Do not administer Armlupeg between 14 days before and 24 hours after administration of chemotherapy.

2.2 Patients with Hematopoietic Subsyndrome of Acute Radiation Syndrome

The recommended dosage of Armlupeg for adults of any weight and pediatric patients weighing at least 45 kg with hematopoietic subsyndrome of acute radiation syndrome is two doses, 6 mg each, administered subcutaneously one week apart. Administer the first dose as soon as possible after suspected or confirmed exposure to radiation levels greater than 2 gray (Gy). Administer the second dose one week after the first dose.

Obtain a baseline complete blood count (CBC). Do not delay administration of Armlupeg if a CBC is not readily available. Estimate a patient's absorbed radiation dose (i.e., level of radiation exposure) based on information from public health authorities, biodosimetry if available, or clinical findings such as time to onset of vomiting or lymphocyte depletion kinetics.

2.3 Preparation and Administration

Armlupeg is supplied in single-dose prefilled syringes for manual use [see Dosage Forms and Strengths (3)].

Before using Armlupeg:

Remove the carton from the refrigerator and allow the Armlupeg prefilled syringe to reach room temperature, 20℃ to 25℃ (68℉ to 77℉), for a minimum of 30 minutes. Do not warm in any other way. Discard any prefilled syringe left at room temperature for greater than 48 hours.

Armlupeg is a clear, colorless, preservative-free solution. Parenteral drug products should be inspected visually for particulate matter and discoloration prior to administration, whenever solution and container permit. Do not administer Armlupeg if discoloration or particulates are observed.

Prefilled Syringe for Manual Use

For adult patients of any weight and pediatric patients weighing 45 kg and greater, the single-dose prefilled syringe for manual use is intended for subcutaneous administration of a single 6 mg/0.6 mL dose of Armlupeg. The syringe does not bear graduation marks and therefore does not allow for direct administration of doses less than 6 mg/0.6 mL. There is no presentation for Armlupeg that allows weight-based dosing for pediatric patients below 45 kg.

The needle cap on the prefilled syringe contains dry natural rubber (derived from latex); persons with latex allergies should not administer this product.

3 DOSAGE FORMS AND STRENGTHS

Armlupeg is a clear, colorless, preservative-free solution available as:

Injection: 6 mg/0.6 mL in a single-dose prefilled syringe for manual use only.

4 CONTRAINDICATIONS

Armlupeg is contraindicated in patients with a history of a serious hypersensitivity reaction to pegfilgrastim products or filgrastim products. Reactions have included anaphylaxis [see Warnings and Precautions (5.3)].

5 WARNINGS AND PRECAUTIONS

5.1 Splenic Rupture

Splenic rupture, including fatal cases, can occur following the administration of pegfilgrastim products. Evaluate for an enlarged spleen or splenic rupture in patients who report left upper abdominal or shoulder pain after receiving Armlupeg.

5.2 Acute Respiratory Distress Syndrome

Acute respiratory distress syndrome (ARDS) can occur in patients receiving pegfilgrastim products. Evaluate patients who develop fever and lung infiltrates or respiratory distress after receiving Armlupeg, for ARDS. Discontinue Armlupeg in patients with ARDS.

5.3 Serious Hypersensitivity Reactions

Serious hypersensitivity reactions, including anaphylaxis, can occur in patients receiving pegfilgrastim products. The majority of reported events occurred upon initial exposure. Hypersensitivity reactions, including anaphylaxis, can recur within days after the discontinuation of initial therapies to manage the reaction. Permanently discontinue Armlupeg in patients with serious hypersensitivity reactions. Armlupeg is contraindicated in patients with a history of a serious hypersensitivity reaction to pegfilgrastim products or filgrastim products.

5.4 Use in Patients with Sickle Cell Disorders

Severe and sometimes fatal sickle cell crises can occur in patients with sickle cell disorders receiving pegfilgrastim products. Discontinue Armlupeg if sickle cell crisis occurs.

5.5 Glomerulonephritis

Glomerulonephritis has occurred in patients receiving pegfilgrastim products. The diagnoses were based upon azotemia, hematuria (microscopic and macroscopic), proteinuria, and renal biopsy. Generally, events of glomerulonephritis resolved after dose‑reduction or discontinuation of pegfilgrastim products. If glomerulonephritis is suspected, evaluate for cause. If causality is likely, consider dose-reduction or interruption of Armlupeg.

5.6 Leukocytosis

White blood cell (WBC) counts of 100×10^9/L or greater have been observed in patients receiving pegfilgrastim products. Monitoring of complete blood count (CBC) during Armlupeg therapy is recommended.

5.7 Thrombocytopenia

Pegfilgrastim products can cause thrombocytopenia. Monitor platelet counts during Armlupeg therapy.

5.8 Capillary Leak Syndrome

Capillary leak syndrome has been reported after G-CSF administration, including pegfilgrastim products, and is characterized by hypotension, hypoalbuminemia, edema and hemoconcentration. Episodes vary in frequency, severity and may be life-threatening if treatment is delayed. Patients who develop symptoms of capillary leak syndrome should be closely monitored and receive standard symptomatic treatment, which may include a need for intensive care.

5.9 Potential for Tumor Growth Stimulatory Effects on Malignant Cells

The granulocyte colony-stimulating factor (G-CSF) receptor through which pegfilgrastim products and filgrastim products act has been found on tumor cell lines. The possibility that pegfilgrastim products acts as a growth factor for any tumor type, including myeloid malignancies and myelodysplasia, diseases for which pegfilgrastim products is not approved, cannot be excluded.

5.10 Myelodysplastic Syndrome (MDS) and Acute Myeloid Leukemia (AML) in Patients with Breast and Lung Cancer

MDS and AML have been associated with the use of pegfilgrastim products in conjunction with chemotherapy and/or radiotherapy in patients with breast and lung cancer. Monitor patients for signs and symptoms of MDS/AML in these settings.

5.11 Aortitis

Aortitis has been reported in patients receiving pegfilgrastim products. It may occur as early as the first week after start of therapy. Manifestations may include generalized signs and symptoms such as fever, abdominal pain, malaise, back pain, and increased inflammatory markers (e.g., c-reactive protein and white blood cell count). Consider aortitis in patients who develop these signs and symptoms without known etiology. Discontinue Armlupeg if aortitis is suspected.

5.12 Nuclear Imaging

Increased hematopoietic activity of the bone marrow in response to growth factor therapy, including pegfilgrastim products, has been associated with transient positive bone imaging changes. This should be considered when interpreting bone imaging results.

6 ADVERSE REACTIONS

The following clinically significant adverse reactions are discussed in greater detail in other sections of the labeling:

- Splenic Rupture [see Warnings and Precautions (5.1)]
- Acute Respiratory Distress Syndrome [see Warnings and Precautions (5.2)]
- Serious Hypersensitivity Reactions [see Warnings and Precautions (5.3)]
- Use in Patients with Sickle Cell Disorders [see Warnings and Precautions (5.4)]
- Glomerulonephritis [see Warnings and Precautions (5.5)]
- Leukocytosis [see Warnings and Precautions (5.6)]
- Thrombocytopenia[see Warnings and Precautions (5.7)]
- Capillary Leak Syndrome [see Warnings and Precautions (5.8)]
- Potential for Tumor Growth Stimulatory Effects on Malignant Cells [see Warnings and Precautions (5.9)]
- Myelodysplastic syndrome [see Warnings and Precautions (5.10)]
- Acute myeloid leukemia [see Warnings and Precautions (5.10)]
- Aortitis[see Warnings and Precautions (5.11)]

6.1 Clinical Trials Experience

Because clinical trials are conducted under widely varying conditions, adverse reaction rates observed in the clinical trials of a drug cannot be directly compared with rates in the clinical trials of another drug and may not reflect the rates observed in clinical practice.

Pegfilgrastim clinical trials safety data are based upon 932 patients receiving pegfilgrastim in seven randomized clinical trials. The population was 21 to 88 years of age and 92% female. The ethnicity was 75% Caucasian, 18% Hispanic, 5% Black, and 1% Asian. Patients with breast (n=823), lung and thoracic tumors (n=53) and lymphoma (n=56) received pegfilgrastim after nonmyeloablative cytotoxic chemotherapy. Most patients received a single 100 mcg/kg (n=259) or a single 6 mg (n= 546) dose per chemotherapy cycle over 4 cycles.

The following adverse reaction data in Table 1 are from a randomized, double-blind, placebo- controlled study in patients with metastatic or non-metastatic breast cancer receiving docetaxel 100 mg/m2 every 21 days (Study 3). A total of 928 patients were randomized to receive either 6 mg pegfilgrastim (n=467) or placebo (n=461). The patients were 21 to 88 years of age and 99% female. The ethnicity was 66% Caucasian, 31% Hispanic, 2% Black, and < 1% Asian, Native American, or other.

The most common adverse reactions occurring in ≥ 5% of patients and with a between-group difference of ≥ 5% higher in the pegfilgrastim arm in placebo-controlled clinical trials are bone pain and pain in extremity.

Table 1. Adverse Reactions with ≥ 5% Higher Incidence in Pegfilgrastim Patients Compared to Placebo in Study 3
Body System Adverse Reaction | Placebo (N = 461) | Pegfilgrastim 6 mg SC on Day 2 (N = 467)
Musculoskeletal and connective tissue disorders
Bone pain | 26% | 31%
Pain in extremity | 4% | 9%

Leukocytosis

In clinical studies, leukocytosis (WBC counts >100x10^9/L) was observed in less than 1% of 932 patients with non-myeloid malignancies receiving Pegfilgrastim. No complications attributable to leukocytosis were reported in clinical studies.

6.3 Postmarketing Experience

The following adverse reactions have been identified during post approval use of Pegfilgrastim products. Because these reactions are reported voluntarily from a population of uncertain size, it is not always possible to reliably estimate their frequency or establish a causal relationship to drug exposure.

- Splenic rupture and splenomegaly (enlarged spleen) [see Warnings and Precautions (5.1)]
- Acute respiratory distress syndrome (ARDS) [see Warnings and Precautions (5.2)]
- Allergic reactions/hypersensitivity, including anaphylaxis, skin rash, urticaria, generalized erythema, and flushing [see Warnings and Precautions (5.3)]
- Sickle cell crisis [see Warnings and Precautions (5.4)]
- Glomerulonephritis [see Warnings and Precautions (5.5)]
- Leukocytosis [see Warnings and Precautions (5.6)]
- Thrombocytopenia[see Warnings and Precautions (5.7)]
- Capillary Leak Syndrome [see Warnings and Precautions (5.8)]
- Injection site reactions
- Sweet's syndrome (acute febrile neutrophilic dermatosis), cutaneous vasculitis
- Myelodysplastic syndrome (MDS) and acute myeloid leukemia (AML) in patients with breast and lung cancer receiving chemotherapy and/or radiotherapy[see Warnings and Precautions (5.10)]
- Aortitis [see Warnings and Precautions (5.11)]
- Alveolar hemorrhage

8 USE IN SPECIFIC POPULATIONS

8.1 Pregnancy

Risk Summary

Although available data with pegfilgrastim product use in pregnant women are insufficient to establish whether there is a drug associated risk of major birth defects, miscarriage, or adverse maternal or fetal outcomes, there are available data from published studies in pregnant women exposed to filgrastim products. These studies have not established an association of filgrastim product use during pregnancy with major birth defects, miscarriage, or adverse maternal or fetal outcomes.

In animal studies, no evidence of reproductive/developmental toxicity occurred in the offspring of pregnant rats that received cumulative doses of pegfilgrastim approximately 10 times the recommended human dose (based on body surface area). In pregnant rabbits, increased embryolethality and spontaneous abortions occurred at 4 times the maximum recommended human dose simultaneously with signs of maternal toxicity (see Data).

The estimated background risk of major birth defects and miscarriage for the indicated population is unknown. All pregnancies have a background risk of birth defect, loss, or other adverse outcomes. In the U.S. general population, the estimated background risks of major birth defects and miscarriage in clinically recognized pregnancies is 2-4% and 15-20%, respectively.

Data

Animal data

Pregnant rabbits were dosed with pegfilgrastim subcutaneously every other day during the period of organogenesis. At cumulative doses ranging from the approximate human dose to approximately 4 times the recommended human dose (based on body surface area), the treated rabbits exhibited decreased maternal food consumption, maternal weight loss, as well as reduced fetal body weights and delayed ossification of the fetal skull; however, no structural anomalies were observed in the offspring from either study. Increased incidences of post-implantation losses and spontaneous abortions (more than half the pregnancies) were observed at cumulative doses approximately 4 times the recommended human dose, which were not seen when pregnant rabbits were exposed to the recommended human dose.

Three studies were conducted in pregnant rats dosed with pegfilgrastim at cumulative doses up to approximately 10 times the recommended human dose at the following stages of gestation: during the period of organogenesis, from mating through the first half of pregnancy, and from the first trimester through delivery and lactation. No evidence of fetal loss or structural malformations was observed in any study. Cumulative doses equivalent to approximately 3 and 10 times the recommended human dose resulted in transient evidence of wavy ribs in fetuses of treated mothers (detected at the end of gestation but no longer present in pups evaluated at the end of lactation).

8.2 Lactation

Risk Summary

There are no data on the presence of pegfilgrastim products in human milk, the effects on the breastfed child, or the effects on milk production. Other filgrastim products are secreted poorly into breast milk, and filgrastim products are not absorbed orally by neonates. The developmental and health benefits of breastfeeding should be considered along with the mother's clinical need for Armlupeg and any potential adverse effects on the breastfed child from Armlupeg or from the underlying maternal condition.

8.4 Pediatric Use

The safety and effectiveness of Armlupeg for chemotherapy-induced neutropenia and hematopoietic subsyndrome of acute radiation syndrome have been established in pediatric patients aged newborn and older.

Use of Armlupeg in pediatric patients for chemotherapy-induced neutropenia is based on adequate and well controlled studies of pegfilgrastim in adults with additional pharmacokinetic and safety data of pegfilgrastim in pediatric patients aged 8 months and older with sarcoma [see Clinical Pharmacology (12.3) and Clinical Studies (14.1)].

The use of Armlupeg to increase survival in pediatric patients acutely exposed to myelosuppressive doses of radiation is based on efficacy studies of pegfilgrastim conducted in animals and clinical data supporting the use of pegfilgrastim in patients with cancer receiving myelosuppressive chemotherapy. Efficacy studies of pegfilgrastim products could not be conducted in humans with acute radiation syndrome for ethical and feasibility reasons. Results from population modeling and simulation indicate that two doses of pegfilgrastim, administered one week apart provide pediatric patients with exposures comparable to that in adults receiving two 6 mg doses one week apart [see Dosage and Administration (2.1, 2.2), Clinical Pharmacology (12.3) and Clinical Studies (14.2)].

8.5 Geriatric Use

Of the 932 patients with cancer who received pegfilgrastim in clinical studies, 139 (15%) were aged 65 and over, and 18 (2%) were aged 75 and over. No overall differences in safety or effectiveness were observed between patients aged 65 and older and younger patients.

10 OVERDOSAGE

Overdosage of pegfilgrastim products may result in leukocytosis and bone pain. Events of edema, dyspnea, and pleural effusion have been reported in a single patient who administered pegfilgrastim on 8 consecutive days in error. In the event of overdose, the patient should be monitored for adverse reactions [see Adverse Reactions (6)]. Consider contacting the Poison Help line (1-800-222-1222) or a medical toxicologist for additional overdose management recommendations.

11 DESCRIPTION

Pegfilgrastim-unne is a covalent conjugate of recombinant methionyl human G-CSF and monomethoxypolyethylene glycol. Recombinant methionyl human G-CSF is a water-soluble 175 amino acid protein with a molecular weight of approximately 19 kilodaltons (kD). Recombinant methionyl human G-CSF is obtained from the bacterial fermentation of a strain of E coli transformed with a genetically engineered plasmid containing the human G-CSF gene. To produce pegfilgrastim-unne, a 20 kD monomethoxypolyethylene glycol molecule is covalently bound to the N-terminal methionyl residue of recombinant methionyl human G-CSF. The average molecular weight of pegfilgrastim-unne is approximately 39 kD.

Armlupeg (pegfilgrastim-unne) injection is a sterile, clear, colorless, preservative-free solution intended for subcutaneous use only and is supplied in a single-dose prefilled syringe with a 27‑gauge ½" needle and rigid needle shield, with UltraSafe Plus PassiveTM Needle Guard. The prefilled syringe does not bear graduation marks and is designed to deliver the entire contents of the syringe (6 mg/0.6 mL).

Each prefilled syringe contains 0.6 mL solution of 6 mg pegfilgrastim-unne (based on protein weight), glacial acetic acid (0.77 mg), polysorbate 20 (0.02 mg), sodium acetate (0.066 mg) and sorbitol (30 mg) in Water for Injection, USP. The pH is 4.

12 CLINICAL PHARMACOLOGY

12.1 Mechanism of Action

Pegfilgrastim products are colony-stimulating factor that acts on hematopoietic cells by binding to specific cell surface receptors, thereby stimulating proliferation, differentiation, commitment, and end cell functional activation.

12.2 Pharmacodynamics

Animal data and clinical data in humans suggest a correlation between pegfilgrastim products' exposure and the duration of severe neutropenia as a predictor of efficacy. Selection of the dosing regimen of Armlupeg is based on reducing the duration of severe neutropenia.

12.3 Pharmacokinetics

The pharmacokinetics of pegfilgrastim was studied in 379 patients with cancer. The pharmacokinetics of pegfilgrastim was nonlinear, and clearance decreased with increases in dose. Neutrophil receptor binding is an important component of the clearance of pegfilgrastim, and serum clearance is directly related to the number of neutrophils. In addition to numbers of neutrophils, body weight appeared to be a factor. Patients with higher body weights experienced higher systemic exposure to pegfilgrastim after receiving a dose normalized for body weight. A large variability in the pharmacokinetics of pegfilgrastim was observed. The half‑life of pegfilgrastim ranged from 15 to 80 hours after subcutaneous injection.

Specific Populations

No gender-related differences were observed in the pharmacokinetics of pegfilgrastim, and no differences were observed in the pharmacokinetics of geriatric patients (≥ 65 years of age) compared with younger patients (< 65 years of age) [see Use in Specific Populations (8.5)].

Renal Impairment

In a study of 30 subjects with varying degrees of renal dysfunction, including end stage renal disease, renal dysfunction had no effect on the pharmacokinetics of pegfilgrastim.

Pediatric Patients with Cancer Receiving Myelosuppressive Chemotherapy

The pharmacokinetics and safety of pegfilgrastim were studied in 37 pediatric patients with sarcoma in Study 4 [see Clinical Studies (14.1)]. The mean (± standard deviation [SD]) systemic exposure (AUC0-inf) of pegfilgrastim after subcutaneous administration at 100 mcg/kg was 47.9 (± 22.5) mcg·hr/mL in the youngest age group (0 to 5 years, n = 11), 22.0 (± 13.1) mcg·hr/mL in the 6 to 11 years age group (n=10), and 29.3 (± 23.2) mcg·hr/mL in the 12 to 21 years age group (n=13). The terminal elimination half-lives of the corresponding age groups were 30.1 (±38.2) hours, 20.2 (±11.3) hours, and 21.2 (±16.0) hours, respectively.

Patients Acutely Exposed to Myelosuppressive Doses of Radiation

The pharmacokinetics of pegfilgrastim products is not available in patients acutely exposed to myelosuppressive doses of radiation. Based on limited pharmacokinetic data in irradiated non-human primates, the area under the concentration-time curve (AUC), reflecting the exposure to pegfilgrastim in non-human primates following a 300 mcg/kg dose of pegfilgrastim, appears to be greater than in humans receiving a 6 mg dose. Results from population modeling and simulation indicate that two 6 mg doses of pegfilgrastim administered one week apart in adults result in clinically relevant effects on duration of grade 3 and 4 neutropenia. In addition, weight based dosing in pediatric patients weighing less than 45 kg provides exposures comparable to those in adults receiving two 6 mg doses one week apart.

12.6 Immunogenicity

The observed incidence of anti-drug antibodies is highly dependent on the sensitivity and specificity of the assay. Differences in assay methods preclude meaningful comparisons of the incidence of anti-drug antibodies in the studies described below with the incidence of anti-drug antibodies in other studies, including those of pegfilgrastim or of other pegfilgrastim products.

Binding antibodies to pegfilgrastim were detected using a BIAcore assay. The approximate limit of detection for this assay is 500 ng/mL. Pre-existing binding antibodies were detected in approximately 6% (51/849) of patients with metastatic breast cancer. Four of 521 pegfilgrastim -treated subjects who were negative at baseline developed binding antibodies to pegfilgrastim following treatment. None of these 4 patients had evidence of neutralizing antibodies detected using a cell-based bioassay.

13 NONCLINICAL TOXICOLOGY

13.1 Carcinogenesis, Mutagenesis, Impairment of Fertility

No carcinogenicity or mutagenesis studies have been performed with pegfilgrastim products.

Pegfilgrastim did not affect reproductive performance or fertility in male or female rats at cumulative weekly doses approximately 6 to 9 times higher than the recommended human dose (based on body surface area).

14 CLINICAL STUDIES

14.1 Patients with Cancer Receiving Myelosuppressive Chemotherapy

Pegfilgrastim was evaluated in three randomized, double-blind, controlled studies. Studies 1 and 2 were active‑controlled studies that employed doxorubicin 60 mg/m^2 and docetaxel 75 mg/m^2 administered every 21 days for up to 4 cycles for the treatment of metastatic breast cancer. Study 1 investigated the utility of a fixed dose of pegfilgrastim. Study 2 employed a weight-adjusted dose. In the absence of growth factor support, similar chemotherapy regimens have been reported to result in a 100% incidence of severe neutropenia (ANC < 0.5x10^9/L) with a mean duration of 5 to 7 days and a 30% to 40% incidence of febrile neutropenia. Based on the correlation between the duration of severe neutropenia and the incidence of febrile neutropenia found in studies with filgrastim, duration of severe neutropenia was chosen as the primary endpoint in both studies, and the efficacy of pegfilgrastim was demonstrated by establishing comparability to filgrastim-treated patients in the mean days of severe neutropenia.

In study 1, 157 patients were randomized to receive a single subcutaneous injection of pegfilgrastim (6 mg) on day 2 of each chemotherapy cycle or daily subcutaneous filgrastim (5 mcg/kg/day) beginning on day 2 of each chemotherapy cycle. In Study 2, 310 patients were randomized to receive a single subcutaneous injection of pegfilgrastim (100 mcg/kg) on day 2 or daily subcutaneous filgrastim (5 mcg/kg/day) beginning on day 2 of each chemotherapy cycle.

Both studies met the major efficacy outcome measure of demonstrating that the mean days of severe neutropenia of pegfilgrastim‑treated patients did not exceed that of filgrastim-treated patients by more than 1 day in cycle 1 of chemotherapy. The mean days of cycle 1 severe neutropenia in Study 1 were 1.8 days in the pegfilgrastim arm compared to 1.6 days in the filgrastim arm [difference in means 0.2 (95% CI - 0.2, 0.6)] and in Study 2 were 1.7 days in the pegfilgrastim arm compared to 1.6 days in the filgrastim arm [difference in means 0.1 (95% CI - 0.2, 0.4)].

A secondary endpoint in both studies was days of severe neutropenia in cycles 2 through 4 with results similar to those for cycle 1.

Study 3 was a randomized, double-blind, placebo-controlled study that employed docetaxel 100 mg/m^2 administered every 21 days for up to 4 cycles for the treatment of metastatic or non-metastatic breast cancer. In this study, 928 patients were randomized to receive a single subcutaneous injection of pegfilgrastim (6 mg) or placebo on day 2 of each chemotherapy cycle. Study 3 met the major trial outcome measure of demonstrating that the incidence of febrile neutropenia (defined as temperature ≥ 38.2°C and ANC ≤ 0.5 x 10^9/L) was lower for pegfilgrastim‑treated patients as compared to placebo-treated patients (1% versus 17%, respectively, p< 0.001). The incidence of hospitalizations (1% versus 14%) and IV anti-infective use (2% versus 10%) for the treatment of febrile neutropenia was also lower in the pegfilgrastim-treated patients compared to the placebo‑treated patients.

Study 4 was a multicenter, randomized, open-label study to evaluate the efficacy, safety, and pharmacokinetics [see Clinical Pharmacology (12.3)] of pegfilgrastim in pediatric and young adult patients with sarcoma. Patients with sarcoma receiving chemotherapy age 0 to 21 years were eligible. Patients were randomized to receive subcutaneous pegfilgrastim as a single dose of 100 mcg/kg (n = 37) or subcutaneous filgrastim at a dose 5 mcg/kg/day (n = 6) following myelosuppressive chemotherapy. Recovery of neutrophil counts was similar in the pegfilgrastim and filgrastim groups. The most common adverse reaction reported was bone pain.

14.2 Patients with Hematopoietic Subsyndrome of Acute Radiation Syndrome

Efficacy studies of pegfilgrastim products could not be conducted in humans with acute radiation syndrome for ethical and feasibility reasons. Approval of this indication was based on efficacy studies conducted in animals and data supporting pegfilgrastim's effect on severe neutropenia in patients with cancer receiving myelosuppressive chemotherapy [see Dosage and Administration (2.1)].

The recommended dose of Armlupeg is two doses, 6 mg each, administered one week apart for humans exposed to myelosuppressive doses of radiation. For pediatric patients weighing less than 45 kg, dosing of Armlupeg is weight based. This dosing regimen is based on population modeling and simulation analyses. The exposure associated with this dosing regimen is expected to provide sufficient pharmacodynamic activity to treat humans exposed to myelosuppressive doses of radiation [see Clinical Pharmacology (12.3)]. The safety of pegfilgrastim at a dose of 6 mg has been assessed on the basis of clinical experience in patients with cancer receiving myelosuppressive chemotherapy.

The efficacy of pegfilgrastim for the acute radiation syndrome setting was studied in a randomized, placebo-controlled non-human primate model of radiation injury. Rhesus macaques were randomized to either a control (n = 23) or treated (n = 23) cohort. On study day 0, animals (n = 6 to 8 per irradiation day) were exposed to total body irradiation (TBI) of 7.50 ± 0.15 Gy delivered at 0.8 ± 0.03 Gy/min, representing a dose that would be lethal in 50% of animals by 60 days of follow-up (LD50/60). Animals were administered subcutaneous injections of a blinded treatment (control article [5% dextrose in water] or pegfilgrastim [300-319 mcg/kg/day]) on study day 1 and on study day 8. The primary endpoint was survival. Animals received medical management consisting of intravenous fluids, antibiotics, blood transfusions, and other support as required.

Pegfilgrastim significantly (at 0.0014 level of significance) increased 60-day survival in irradiated non-human primates: 91% survival (21/23) in the pegfilgrastim group compared to 48% survival (11/23) in the control group.

16 HOW SUPPLIED/STORAGE AND HANDLING

Armlupeg (pegfilgrastim-unne) injection is a clear, colorless solution supplied in a prefilled single-dose syringe for manual use containing 6 mg pefilgrastim-unne, supplied with a 27-gauge, 1/2-inch needle with an UltraSafe® Plus PassiveTM Needle Guard.

The needle cap of the prefilled syringe contains dry natural rubber (a derivative of latex).

Armlupeg is provided in a carton containing one sterile 6 mg/0.6 mL prefilled syringe (NDC 70748-273-01).

Armlupeg prefilled syringe does not bear graduation marks and is intended only to deliver the entire contents of the syringe (6 mg/0.6 mL) for direct administration.

Store refrigerated between 2°C to 8°C (36°F to 46°F) in the original carton to protect from light. Do not shake. Discard syringes stored at room temperature for more than 48 hours. Avoid freezing; if frozen, thaw in the refrigerator before administration. Discard syringe if frozen more than once.

17 PATIENT COUNSELING INFORMATION

Advise the patient to read the FDA-approved patient labeling (Patient Information and Instructions for Use).

Advise patients of the following risks and potential risks with Armlupeg:

- Splenic rupture and splenomegaly
- Acute Respiratory Distress Syndrome
- Serious hypersensitivity reactions
- Sickle cell crisis
- Glomerulonephritis
- Increased risk of Myelodysplastic Syndrome and/or Acute Myeloid Leukemia in patients with breast and lung cancer who receive Armlupeg in conjunction with chemotherapy and/or radiation therapy.
- Capillary Leak Syndrome
- Aortitis

Advise patients acutely exposed to myelosuppressive doses of radiation (Hematopoietic Subsyndrome of Acute Radiation Syndrome) that efficacy studies of pegfilgrastim products for this indication could not be conducted in humans for ethical and feasibility reasons and that, therefore, approval of this use was based on efficacy studies conducted in animals [see Clinical Studies (14.2)].

Instruct patients who self-administer Armlupeg using the single-dose prefilled syringe of the:

- Importance of following the Instructions for Use.
- Dangers of reusing syringes.
- Importance of following local requirements for proper disposal of used syringes.

ARMLUPEG®(pegfilgrastim-unne)

Manufactured for:

Lupin Pharmaceuticals, Inc.

Naples, FL 34108 United States

Manufactured by:

Lupin Limited (Biotech Division)

Gat No. 1156, 1157, 1158, 1159 and 1160,

Village-Ghotawade, Taluka-Mulshi,

Pune – 412115, Maharashtra, India

Distributed by:

Valorum Biologics, LLC

555 Madison Ave. Suite 11D

New York, NY USA 10022

US License No. 2052

Patient Information
ARMLUPEG® (arm loo peg)
(pegfilgrastim-unne)
injection
Single-Dose Prefilled Syringe

What is Armlupeg?
Armlupeg is a prescription medicine that is used:
in adults and children aged newborn and older to help reduce the chance of infection due to a low white blood cell count, in people with certain types of cancer (non-myeloid), who receive anti-cancer medicines (chemotherapy) that can cause fever and low blood cell count.
in adults and children aged newborn and older for acute radiation syndrome. The effectiveness of pegfilgrastim for this use was only studied in animals, because it could not be studied in people.

Do not take Armlupeg if you have had a serious allergic reaction to pegfilgrastim products or filgrastim products.

Before you receive Armlupeg, tell your healthcare provider about all of your medical conditions, including if you:
have a sickle cell disorder.
have kidney problems.
are allergic to latex. The needle cap on the prefilled syringe contains dry natural rubber (derived from latex). You should not give Armlupeg using the prefilled syringe if you have latex allergies.
are pregnant or plan to become pregnant. It is not known if Armlupeg will harm your unborn baby.
are breastfeeding or plan to breastfeed. It is not known if Armlupeg passes into your breast milk.
Tell your healthcare provider about all of the medicines you take, including prescription and over-the counter medicines, vitamins, and herbal supplements.

How will I receive Armlupeg?
Armlupeg is given as an injection under your skin (subcutaneous injection) by a healthcare provider. If your healthcare provider decides that the subcutaneous injections can be given at home by you or your caregiver, follow the detailed "Instructions for Use" that comes with your Armlupeg for information on how to prepare and inject a dose of Armlupeg using the single-dose prefilled syringe.
You and your caregiver will be shown how to prepare and inject Armlupeg using the single-dose prefilled syringe before you use it.
You should not inject a dose of Armlupeg to children weighing less than 99 pounds (45 kg) from an Armlupeg prefilled syringe.
If you are receiving Armlupeg because you are also receiving chemotherapy, the last dose of Armlupeg should be injected at least 14 days before and 24 hours after your dose of chemotherapy.
If you miss a dose of Armlupeg, talk to your healthcare provider about when you should give your next dose.
If you inject too much Armlupeg, call your healthcare provider or Poison Help line at 1-800-222-1222 or go to the nearest hospital emergency room right away.

What are possible side effects of Armlupeg?
Armlupeg may cause serious side effects, including:
Spleen rupture. Your spleen may become enlarged and can rupture. A ruptured spleen can cause death. Call your healthcare provider right away if you have pain in the left upper stomach area or your left shoulder.
A serious lung problem called Acute Respiratory Distress Syndrome (ARDS). Call your healthcare provider or get emergency help right away if you have shortness of breath with or without a fever, trouble breathing, or a fast rate of breathing.
Serious allergic reactions. Allergic reactions can cause a rash over your whole body, shortness of breath, wheezing, dizziness, swelling around your mouth or eyes, fast heart rate, and sweating. If you have any of these symptoms, stop using Armlupeg and call your healthcare provider or get emergency medical help right away.
Sickle cell crises in people with sickle cell disorder. You may have a severe sickle cell crisis, which could lead to death. Call your healthcare provider right away if you have symptoms of sickle cell crisis such as pain or difficulty breathing.
Kidney injury. Call your healthcare provider right away if you develop any of the following symptoms:

- swelling of your face or ankles
- blood in your urine or dark colored urine
- you urinate less than usual

Increased white blood cell count (leukocytosis). Your healthcare provider will check your blood count during treatment with Armlupeg.
Decreased platelet count (thrombocytopenia). Your healthcare provider will check your blood count during treatment with Armlupeg. Tell your healthcare provider if you have unusual bleeding or bruising during treatment with Armlupeg.
Capillary Leak Syndrome (CLS). Armlupeg can cause fluid to leak from blood vessels into your body's tissues. CLS can quickly cause you to have symptoms that may become life-threatening. Get emergency medical help right away if you develop any of the following symptoms:

- swelling or puffiness and are urinating less than usual
- trouble breathing
- swelling of your stomach area (abdomen) and feeling of fullness
- dizziness or feeling faint
- a general feeling of tiredness

Myelodysplastic Syndrome (MDS) and Acute Myeloid Leukemia (AML). If you have breast cancer or lung cancer, when Armlupeg is used with chemotherapy and radiation therapy, or with radiation therapy alone, you may have an increased risk of developing a precancerous blood condition called MDS or a blood cancer called AML. Call your healthcare provider if you develop any symptoms of MDS and AML, including tiredness, fever, or easy bruising or bleeding.
Inflammation of the aorta (aortitis) . Inflammation of the aorta (the large blood vessel that carries blood from the heart to the body) has happened in people who receive pegfilgrastim products. Tell your healthcare provider if you develop fever, stomach (abdominal) pain, feeling tired, or back pain.
The most common side effects of Armlupeg are pain in the bones, arms, and legs.
These are not all the possible side effects of Armlupeg.
Call your healthcare provider for medical advice about side effects. You may report side effects to FDA at 1-800-FDA-1088.

How should I store Armlupeg single-dose prefilled syringes?
Store Armlupeg in the refrigerator between 36°F to 46°F (2°C to 8°C).
Do not freeze. If Armlupeg is accidentally frozen, allow the prefilled syringe to thaw in the refrigerator before injecting.
Do not use an Armlupeg prefilled syringe that has been frozen more than 1 time. Throw it away and use a new Armlupeg prefilled syringe.
Keep Armlupeg in the original carton to protect from light or physical damage.
Do not shake Armlupeg.
Take Armlupeg out of the refrigerator 30 minutes before use and allow it to reach room temperature, 68°F to 77°F (20°C to 25°C), before preparing an injection.
Throw away (dispose of) any Armlupeg that has been left at room temperature, 68°F to 77°F (20°C to 25°C), for more than 48 hours.
Keep Armlupeg and all medicines out of the reach of children.

General information about the safe and effective use of Armlupeg.
Medicines are sometimes prescribed for purposes other than those listed in a Patient Information leaflet. Do not use Armlupeg for a condition for which it was not prescribed. Do not give Armlupeg to other people, even if they have the same symptoms that you have. It may harm them. You can ask your pharmacist or healthcare provider for information about Armlupeg that is written for health professionals.

What are the ingredients in Armlupeg?
Active ingredient : pegfilgrastim-unne
Inactive ingredients : glacial acetic acid, polysorbate 20, sodium acetate, sorbitol in Water for Injection.
Manufactured for:
Lupin Pharmaceuticals, Inc.
Naples, FL 34108 United States
Manufactured by:
Lupin Limited (Biotech Division)
Gat No. 1156, 1157, 1158, 1159 and 1160,
Village-Ghotawade, Taluka-Mulshi,
Pune – 412115, Maharashtra, India
Distributed by:
Valorum Biologics, LLC
555 Madison Ave. Suite 11D
New York, NY USA 10022
US License No. 2052
For more information go to www.lupin.com or call 1-800-399-2561.

INSTRUCTIONS FOR USE SECTION

Instructions for Use

ARMLUPEG® (arm loo peg)

(pegfilgrastim-unne)

injection, for subcutaneous use

Single-Dose Prefilled Syringe

Guide to parts

Important: The needle is covered by the gray needle cap before use.

Important

Read the Patient Information for important information you need to know about Armlupeg before using these Instructions for Use.

Before you use an Armlupeg prefilled syringe, read this important information.

Storing the prefilled syringe

Store Armlupeg in the refrigerator between 36°F to 46° F (2°C to 8°C).

Do not freeze. If Armlupeg is accidentally frozen, allow the prefilled syringe to thaw in the refrigerator before injecting.

Do not use an Armlupeg prefilled syringe that has been frozen more than 1 time. Throw it away and use a new Armlupeg prefilled syringe.

Keep the prefilled syringe in the original carton to protect from light or physical damage.

Take the prefilled syringe out of the refrigerator 30 minutes before use and allow it to reach room temperature, 68°F to 77°F (20°C to 25°C), before preparing an injection.

Throw away (dispose of) any Armlupeg that has been left at room temperature, 68°F to 77°F (20°C to 25°C), for more than 48 hours.

Keep Armlupeg and all medicines out of the reach of children.

Using the prefilled syringe

It is important that you do not try to give the injection unless you or your caregiver has received training from your healthcare provider.

Make sure the name Armlupeg appears on the carton and prefilled syringe label.

Check the carton and prefilled syringe label to make sure the dose strength is 6 mg.

You should not inject a dose of Armlupeg to children weighing less than 99 pounds (45 kg) from an Armlupeg prefilled syringe.

Do not use a prefilled syringe after the expiration date on the label.

Do not shake the prefilled syringe.

Do not remove the gray needle cap from the prefilled syringe until you are ready to inject.

Do not use the prefilled syringe if the carton is open or damaged.

Do not use a prefilled syringe if it has been dropped on a hard surface. The prefilled syringe may be broken even if you cannot see the break. Use a new prefilled syringe.

Do not attempt to activate the needle safety guard prior to injection. Do not use the prefilled syringe if the needle safety guard has been activated. Use another prefilled syringe that has not been activated and is ready to use.

The gray needle cap on the prefilled syringe contains dry natural rubber (made from latex). Tell your healthcare provider if you are allergic to latex. You should not give Armlupeg using the prefilled syringe if you have latex allergies.

Call your healthcare provider if you have any questions.

STEP 1: Prepare

A. Remove the prefilled syringe carton from refrigerator.

Check the expiration date printed on the carton.

Important: Do not use if the expiration date has passed.

Remove the syringe tray from the carton. On a clean, well-lit surface, place the syringe tray at room temperature for 30 minutes before you give an injection.

Do not remove the prefilled syringe from the original carton until you are ready to inject.

Do not use the prefilled syringe if the carton is damaged.

Do not try to warm the prefilled syringe by using a heat source such as hot water or microwave.

Do not leave the prefilled syringe in direct sunlight.

Do not shake the prefilled syringe.

Open the tray by peeling away the cover. Grab the safety guard to remove the prefilled syringe from the tray. (See Figure 3)

For Safety reasons:

B. Inspect the medicine and prefilled syringe (See Figure 4).

Make sure the medicine in prefilled syringe is clear and colorless (See Figure 4). It is normal to see one or more air bubbles in the syringe.

Do not use the prefilled syringe if:

The medicine is cloudy or discolored or contains flakes or particles.

Any part appears cracked or broken.

The prefilled syringe has been dropped.

The gray needle cap is missing or not securely attached.

The expiration date printed on the label has passed.

In all cases, use a new prefilled syringe and call your healthcare provider.

C. Gather all materials needed for injection (See Figure 5)

Wash your hands thoroughly with soap and water

On a clean, well-lit work surface, place the:

Prefilled syringe

Alcohol swab

Cotton ball or gauze pad

Adhesive bandage

Sharps disposal container

STEP 2: Get ready

D. Select and clean the injection site (See Figures 6 and 7).

You can use:

Clean the injection site with an alcohol swab (See Figure 7). Let the skin dry.

Do not touch this area again before injecting.

If you want to use the same injection site, make sure it is not the same spot on the injection site you used for a previous injection.

Do not inject into areas where the skin is tender, bruised, red, or hard. Avoid injecting into areas with scars or stretch marks.

E. Hold the prefilled syringe by the syringe body. Carefully pull the gray needle cap straight off and away from the body (See Figure 8).

Do not remove the gray needle cap from the prefilled syringe until you are ready to inject.

Do not twist or bend the needle cap.

Do not hold the prefilled syringe by the plunger rod

Do not put the gray needle cap back onto the syringe or never recap. If the needle cap is removed accidently and you are not ready for the injection, discard (throw away) the opened syringe and use a new syringe when ready.

Important: Throw the gray needle cap into the sharps disposal container (See Figure 9).

Step 3: Subcutaneous (under the skin) injection

F. Point the needle up and gently tap the syringe body with your fingers until the air bubble rises to the top of the syringe (See Figure 10).

G. Pinch the injection site to create a firm surface (See Figure 11).

Important: Keep skin pinched while injecting

H. Hold the pinch. Insert the needle into the skin at 45 to 90 degrees. (See Figure 12)

Do not touch the plunger rod or grasp the syringe above the finger grips.

I. Using slow and constant pressure, push the plunger head until it reaches the bottom. (See Figure 13)

While the needle is still inserted in the skin, slowly move your thumb back, allowing the plunger rod to rise. This will release the needle safety guard to safely cover the needle. Then remove the syringe from the injection site. (See Figure 14)

Important: When you remove the syringe, if it looks like the needle safety guard is not activated or some medicine is still left in the syringe, this means you have not received a full dose. Call your healthcare provider right away.

Step 4: Finish

J. For your safety, make sure that the needle safety guard is activated and fully covers the needle.

Once the needle safety guard is extended, it will lock into position and will not slide back over the needle.

Important: Keep your hands away from the needle at all times.

K. Discard (throw away) the used prefilled syringe.

Put the used prefilled syringe into an FDA-cleared sharps disposal container right away after use (See Figure 15). Do not throw away (dispose of) the syringe in the household trash.

If you do not have an FDA-cleared sharps disposal container, you may use a household container that is:

o made of a heavy-duty plastic,

o can be closed with a tight-fitting, puncture-resistant lid, without sharps being able to come out,

o upright and stable during use,

o leak-resistant, and

o properly labeled to warn of hazardous waste inside the container.

When your sharps disposal container is almost full, you will need to follow your community guidelines for the right way to dispose of your sharps disposal container. There may be state or local laws about how you should throw away used needles and syringes. For more information about safe sharps disposal, and for specific information about sharps disposal in the state that you live in, go to the FDA's website at: http://www.fda.gov/safesharpsdisposal.

Do not reuse the prefilled syringe.

Do not recycle prefilled syringes or sharps disposal container or throw them into household trash.

Important: Always keep the sharps disposal container out of the reach of children.

L. Examine the injection site.

If there is blood, press a cotton ball or gauze pad on the injection site. Do not rub the injection site. Apply an adhesive bandage if needed.

This Instructions for Use has been approved by the U.S. Food and Drug Administration.

Manufactured for:

Lupin Pharmaceuticals, Inc.

Naples, FL 34108 United States.

Manufactured by:

Lupin Limited (Biotech Division)

Gat No. 1156, 1157, 1158, 1159 and 1160,

Village-Ghotawade, Taluka-Mulshi,

Pune – 412115, Maharashtra, India

Distributed by:

Valorum Biologics, LLC

555 Madison Ave. Suite 11D

New York, NY USA 10022

U.S. License No. 2052

Approved: November 2025

PACKAGE LABEL.PRINCIPAL DISPLAY PANEL - SYRINGE LABEL

NDC 70748-273-01

Armlupeg®

(pegfilgrastim-unne) Injection

6 mg/0.6 mL

For Subcutaneous Use Only

Single-Dose Prefilled Syringe

Rx Only

LOT

NO.

EXP.

M.L.: 28D-PD/Vacc/12

Manufactured by:

Lupin Limited (Biotech Division)

Gat No. 1156, 1157, 1158, 1159 and 1160,

Village-Ghotawade, Taluka-Mulshi,

Pune - 412115,

Maharashtra, India

U.S. License No. 2052

PACKAGE LABEL.PRINCIPAL DISPLAY PANEL - CARTON LABEL

NDC 70748-273-01

Armlupeg®

(pegfilgrastim-unne) Injection

6 mg/0.6 mL

For Subcutaneous Use Only

Pegylated Recombinant Methionyl Human Granulocyte Colony

Stimulating Factor (PEG-r-metHuG-CSF) derived from E. coli

One 0.6 mL Single-Dose Prefilled Syringe

RX Only